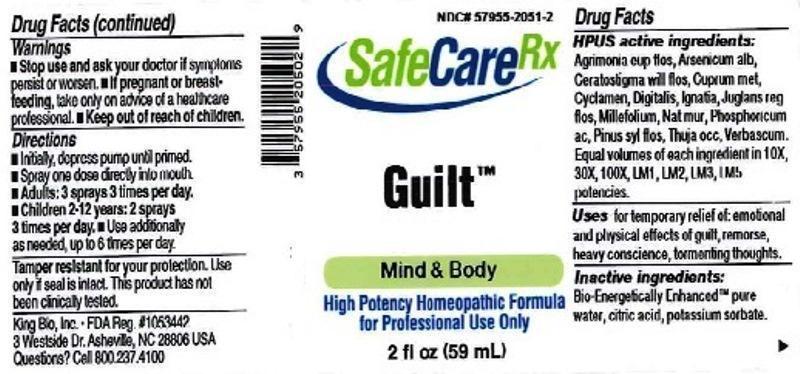 DRUG LABEL: Guilt
NDC: 57955-2051 | Form: LIQUID
Manufacturer: King Bio Inc.
Category: homeopathic | Type: HUMAN OTC DRUG LABEL
Date: 20150616

ACTIVE INGREDIENTS: AGRIMONIA EUPATORIA FLOWER 10 [hp_X]/59 mL; ARSENIC TRIOXIDE 10 [hp_X]/59 mL; CERATOSTIGMA WILLMOTTIANUM FLOWER 10 [hp_X]/59 mL; COPPER 10 [hp_X]/59 mL; CYCLAMEN PURPURASCENS TUBER 10 [hp_X]/59 mL; DIGITALIS 10 [hp_X]/59 mL; STRYCHNOS IGNATII SEED 10 [hp_X]/59 mL; JUGLANS REGIA FLOWERING TOP 10 [hp_X]/59 mL; ACHILLEA MILLEFOLIUM 10 [hp_X]/59 mL; SODIUM CHLORIDE 10 [hp_X]/59 mL; PHOSPHORIC ACID 10 [hp_X]/59 mL; PINUS SYLVESTRIS LEAFY TWIG 10 [hp_X]/59 mL; THUJA OCCIDENTALIS LEAFY TWIG 10 [hp_X]/59 mL; VERBASCUM THAPSUS 10 [hp_X]/59 mL
INACTIVE INGREDIENTS: WATER; ANHYDROUS CITRIC ACID; POTASSIUM SORBATE

Guilt™

ACTIVE INGREDIENT

Drug Facts__________________________________________________________________________________________________________

HPUS active ingredients: Agrimonia eupatoria, flos, Arsenicum album, Ceratostigma willmottianum, flos, Cuprum metallicum, Cyclamen europaeum, Digitalis purpurea, Ignatia amara, Juglans regia, flos, Millefolium, Natrum muriaticum, Phosphoricum acidum, Pinus sylvestris, Thuja occidentalis, Verbascum thapsus. Equal volumes of each ingredient in 10X, 30X, 100X, LM1, LM2, LM3, LM5 potencies.

INDICATIONS AND USAGE

Uses for temporary relief of: emotional and physical effects of guilt, remorse, heavy conscience, tormenting thoughts.

INACTIVE INGREDIENT

Inactive Ingredients: Bio-Energetically Enhanced™ pure water, citric acid and potassium sorbate.

Warnings

- Stop use and ask your doctor if symptoms persist or worsen.
- If pregnant or breast-feeding, take only on advice of a healthcare professional.

- Keep out of reach of children.

Directions

- Initially, depress pump until primed.
- Spray one dose directly into mouth.
- Adults: 3 sprays 3 times per day.
- Children 2-12 years: 2 sprays 3 times per day.
- Use additionally as needed, up to 6 times per day.

OTHER SAFETY INFORMATION

Tamper resistant for your protection. Use only if safety seal is intact. This product has not been clinically tested.

PURPOSE

Uses for temporary relief of:

- emotional and physical effects of guilt
- remorse
- heavy conscience
- tormenting thoughts